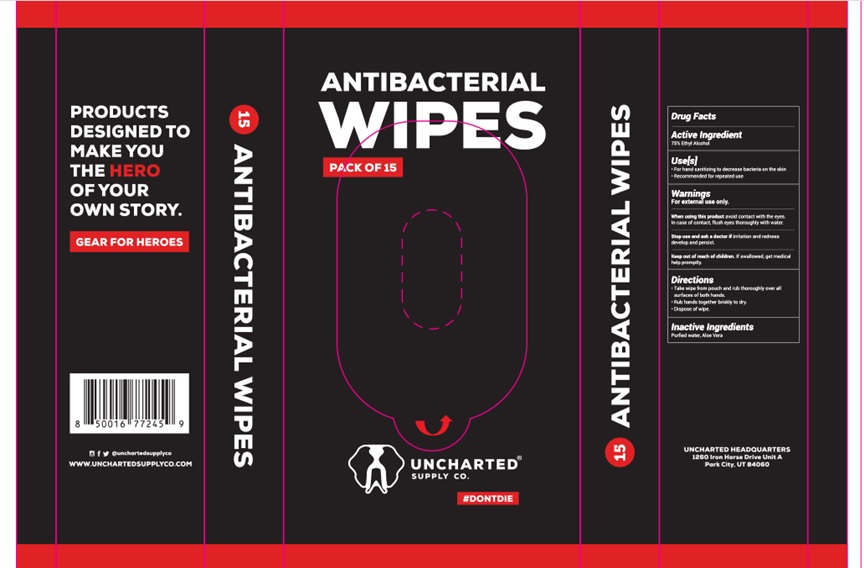 DRUG LABEL: 15pcs Antibactrial Wipes
NDC: 71734-106 | Form: SWAB
Manufacturer: JIANGMEN SHUIZIRUN SANITARY ARTICLES CO., LTD.
Category: otc | Type: HUMAN OTC DRUG LABEL
Date: 20211210

ACTIVE INGREDIENTS: Alcohol 75 g/100 g
INACTIVE INGREDIENTS: water

DRUG FACTS

Active Ingredient

Ethly Alcohol ................ 75%

Purpose

Antiseptic Cleanser

Uses:

For hand sanitizing to decrease bacteria on the skin; Recommended for repeated use.

Warnings

For external use only.

- When using this product avoid contact with the eyes. In case of contact,flush eyes thoroughly with water ;
- Stop use and ask a doctor if irritation and redness develop and persist.

Keep out of reach of children.

if swallowed get medical help or contact a Poison Control Center right away.

Directions

Take wipe from pouch and rub thoroughly over all surfaces of both hands.

Rub hands together briskly to dry.

Disopose of wipe.

Inactive Ingredients:

Purified Water